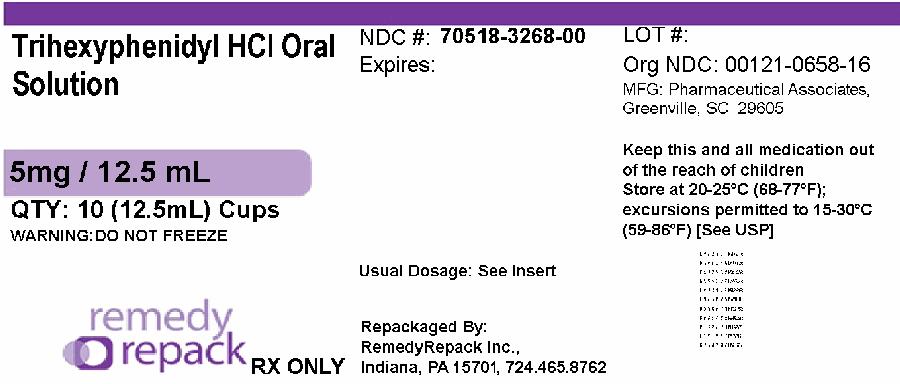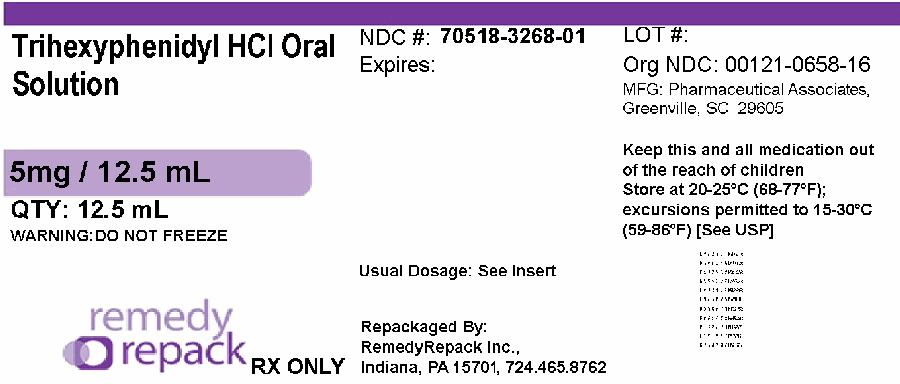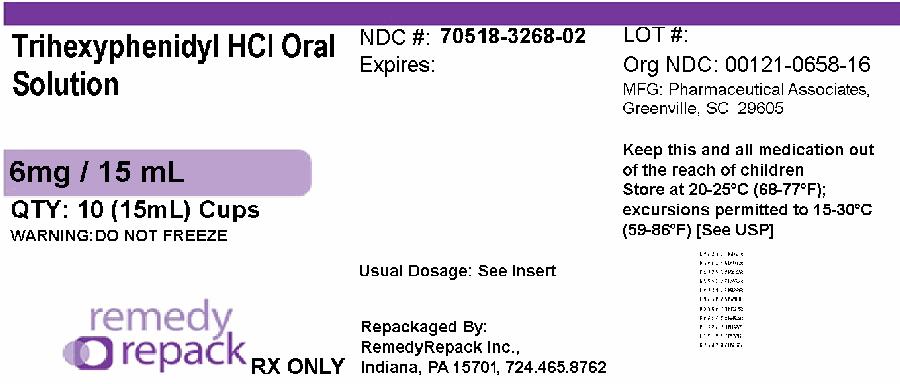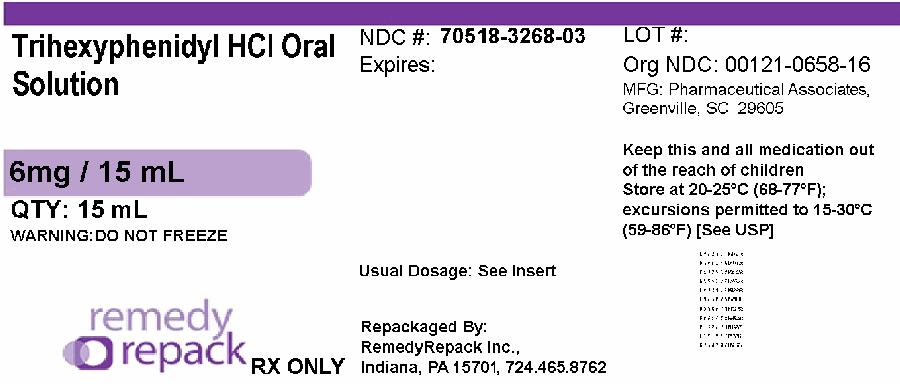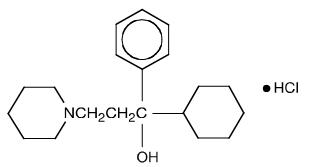 DRUG LABEL: Trihexyphenidyl Hydrochloride
NDC: 70518-3268 | Form: SOLUTION
Manufacturer: REMEDYREPACK INC.
Category: prescription | Type: HUMAN PRESCRIPTION DRUG LABEL
Date: 20250718

ACTIVE INGREDIENTS: TRIHEXYPHENIDYL HYDROCHLORIDE 2 mg/5 mL
INACTIVE INGREDIENTS: PROPYLPARABEN; WATER; SODIUM CHLORIDE; ALCOHOL; METHYLPARABEN; ANHYDROUS CITRIC ACID; SORBITOL SOLUTION

Trihexyphenidyl Hydrochloride Oral Solution USP
2 mg per 5 mL

Rx ONLY

DESCRIPTION

Trihexyphenidyl Hydrochloride Oral Solution USP is a synthetic antispasmodic drug. It is designated chemically as α-Cyclohexylα-phenyl-1-piperidinepropanol hydrochloride and its structural formula is as follows:

Trihexyphenidyl hydrochloride occurs as a white or creamy-white, almost odorless, crystalline powder. It is very slightly soluble in ether and benzene, slightly soluble in water and soluble in methanol.

Each 5 mL (teaspoonful) for oral administration contains 2 mg trihexyphenidyl hydrochloride and alcohol 5% in a clear, colorless, lime-mint flavored solution. In addition, it contains the following inactive ingredients: citric acid, flavoring, methylparaben, propylparaben, purified water, sodium chloride and sorbitol solution.

CLINICAL PHARMACOLOGY

Trihexyphenidyl exerts a direct inhibitory effect upon the parasympathetic nervous system. It also has a relaxing effect on smooth musculature; exerted both directly upon the muscle tissue itself and indirectly through an inhibitory effect upon the parasympathetic nervous system. Its therapeutic properties are similar to those of atropine although undesirable side effects are ordinarily less frequent and severe than with the latter.

INDICATIONS AND USAGE

Trihexyphenidyl is indicated as an adjunct in the treatment of all forms of parkinsonism (postencephalitic, arteriosclerotic, and idiopathic). It is often useful as adjuvant therapy when treating these forms of parkinsonism with levodopa. Additionally, it is indicated for the control of extrapyramidal disorders caused by central nervous system drugs such as the dibenzoxazepines, phenothiazines, thioxanthenes, and butyrophenones.

CONTRAINDICATIONS

Trihexyphenidyl is contraindicated in patients with hypersensitivity to trihexyphenidyl or to any of the other ingredients. Trihexyphenidyl is also contraindicated in patients with narrow angle glaucoma. Blindness after long-term use due to narrow angle glaucoma has been reported.

WARNINGS

Patients to be treated with trihexyphenidyl should have a gonioscope evaluation prior to initiation of therapy and close monitoring of intraocular pressures. The use of anticholinergic drugs may precipitate angle closure with an increase in intraocular pressure. If blurring of vision occurs during therapy, the possibility of narrow angle glaucoma should be considered. Blindness has been reported due to aggravation of narrow angle glaucoma. (See CONTRAINDICATIONSand ADVERSE REACTIONS).

Trihexyphenidyl should be administered with caution in hot weather, especially when given concomitantly with other atropine-like drugs to the chronically ill, alcoholics, those who have central nervous system disease, or those who do manual labor in a hot environment. Anhidrosis may occur more readily when some disturbance of sweating already exists. If there is evidence of anhidrosis, the possibility of hyperthermia should be considered. Dosage should be decreased so that the ability to maintain body heat equilibrium via perspiration is not impaired. Severe anhidrosis and fatal hyperthermia have occurred with the use of anticholinergics under the conditions described above.

Neuroleptic Malignant Syndrome

A potentially fatal symptom complex sometimes referred to as Neuroleptic Malignant Syndrome (NMS) has been reported in association with dose reduction or discontinuation of trihexyphenidyl. Clinical manifestations of NMS are hyperpyrexia, muscle rigidity, altered mental status and evidence of autonomic instability (irregular pulse or blood pressure, tachycardia, diaphoresis and cardiac dysrhythmias).

The diagnostic evaluation of patients with this syndrome is complicated. In arriving at a diagnosis, it is important to identify cases where the clinical presentation includes both serious medical illness (e.g., pneumonia, systemic infection, etc.) and untreated or inadequately treated extrapyramidal signs and symptoms (EPS). Other important considerations in the differential diagnosis include central anticholinergic toxicity, heat stroke, drug fever, and primary central nervous system (CNS) pathology.

PRECAUTIONS

General

Patients with cardiac, liver, or kidney disorders, or with hypertension, should be closely monitored.

Since trihexyphenidyl has atropine-like properties, patients on long-term treatment should be carefully monitored for untoward reactions.

Since trihexyphenidyl has parasympatholytic activity, it should be used with caution in patients with glaucoma, obstructive disease of the gastrointestinal or genitourinary tracts, and in elderly males with possible prostatic hypertrophy. Incipient glaucoma may be precipitated by parasympatholytic drugs such as trihexyphenidyl.

Tardive dyskinesia may appear in some patients on long-term therapy with antipsychotic drugs or may occur after therapy with these drugs has been discontinued. Antiparkinsonism agents do not alleviate the symptoms of tardive dyskinesia, and in some instances may aggravate them.

However, parkinsonism and tardive dyskinesia often coexist in patients receiving chronic neuroleptic treatment, and anticholinergic therapy with trihexyphenidyl may relieve some of these parkinsonism symptoms. Trihexyphenidyl is not recommended for use in patients with tardive dyskinesia unless they have concomitant Parkinson's disease.

Patients with arteriosclerosis or with a history of idiosyncrasy to other drugs may exhibit reactions of mental confusion, agitation, disturbed behavior, or nausea and vomiting. Such patients should be allowed to develop a tolerance through the initial administration of a small dose and gradual increase in dose until an effective level is reached. If a severe reaction should occur, administration of the drug should be discontinued for a few days and then resumed at a lower dosage. Psychiatric disturbances can result from indiscriminate use (leading to overdosage) to sustain continued euphoria. (See DRUG ABUSE AND DEPENDENCE).

Abrupt withdrawal of treatment for parkinsonism may result in acute exacerbation of parkinsonism symptoms; therefore, abrupt withdrawal should be avoided (See DOSAGE AND ADMINISTRATION).

Information for Patients

Trihexyphenidyl may impair mental and/or physical abilities required for performance of hazardous tasks, such as operating machinery or driving a motor vehicle. Patients should be cautioned about operating machinery, including automobiles, until they are reasonably certain that trihexyphenidyl therapy does not adversely affect their ability to engage in such activities.

Because of increased sedative effects, patients should be cautioned to avoid the use of alcohol or other CNS depressants while taking trihexyphenidyl.

Since this medication may increase the susceptibility to heat stroke (gastrointestinal (GI) problems, fever, heat intolerance), use with caution during hot weather. (See WARNINGS).

Patients should be advised to report the occurrence of GI problems, fever, or heat intolerance promptly since paralytic ileus, hyperthermia, or heat stroke may occur.

If GI upset occurs, trihexyphenidyl may be taken with food.

Patients should have close monitoring of intraocular pressure. (See WARNINGS).

Repackaged By / Distributed By: RemedyRepack Inc.

625 Kolter Drive, Indiana, PA 15701

(724) 465-8762

Drug Interactions

Cannabinoids, barbiturates, opiates, and alcohol may have additive effects with trihexyphenidyl, and thus, an abuse potential exists.

Concurrent use of alcohol or other CNS depressants with trihexyphenidyl may cause increased sedative effects.

Monoamine oxidase inhibitors and tricyclic antidepressants possessing significant anticholinergic activity may intensify the anticholinergic effects of antidyskinetic agents because of the secondary anticholinergic activities of these medications.

Prophylactic administration of anticholinergic agents, such as trihexyphenidyl, as a prevention of drug-induced parkinsonism during neuroleptic therapy is not recommended. There may be an increased risk for the development of tardive dyskinesia during concomitant administration of anticholinergics and neuroleptics (See PRECAUTIONS, General).

The usual dose of either trihexyphenidyl or levodopa may need to be reduced during concomitant therapy, since concomitant administration may increase drug-induced involuntary movements (See DOSAGE AND ADMINISTRATION).

Carcinogenesis, Mutagenesis, Impairment of Fertility

No carcinogenicity studies or adequate genotoxicity or fertility studies have been conducted for trihexyphenidyl.

Pregnancy

TERATOGENIC EFFECTS

Animal reproduction studies to evaluate teratogenic and embryotoxic potential have not been conducted with trihexyphenidyl. It is also not known whether trihexyphenidyl can cause fetal harm when administered to a pregnant woman or can affect reproduction capacity. Trihexyphenidyl should be given to a pregnant woman only if clearly needed.

Nursing Mothers

It is not known whether this drug is excreted in human milk. Because many drugs are excreted in human milk, caution should be exercised when trihexyphenidyl is administered to a nursing woman.

As with other anticholinergics, trihexyphenidyl may cause suppression of lactation. Therefore, trihexyphenidyl should only be used if the expected benefit to the mother outweighs the potential risk to the infant.

Pediatric Use

Safety and effectiveness in pediatric patients have not been established. (See also ADVERSE REACTIONS).

Geriatric Use

Sensitivity to the actions of parasympatholytic drugs may increase with age, particularly over the age of 60; therefore, elderly patients generally should be started on low doses of trihexyphenidyl and observed closely. Trihexyphenidyl has been shown to cause some cognitive dysfunctions in the elderly, including confusion and memory impairment. (See ADVERSE REACTIONSand DOSAGE AND ADMINISTRATION).

ADVERSE REACTIONS

Minor side effects, such as dryness of the mouth, blurred vision, dizziness, mild nausea or nervousness, will be experienced by 30 to 50 percent of all patients. These sensations, however, are much less troublesome with trihexyphenidyl than with belladonna alkaloids and are usually less disturbing than unalleviated parkinsonism. Such reactions tend to become less pronounced, and even to disappear, as treatment continues. Even before these reactions have remitted spontaneously, they may often be controlled by careful adjustment of dosage form, amount of drug, or interval between doses.

Isolated instances of suppurative parotitis secondary to excessive dryness of the mouth, skin rashes, dilatation of the colon, paralytic ileus, and certain psychiatric manifestations such as delusions, hallucinations, and paranoia, all of which may occur with any of the atropine-like drugs, have been reported rarely with trihexyphenidyl.

Potential side effects associated with the use of any atropine-like drugs, including trihexyphenidyl, include cognitive dysfunctions, including confusion and memory impairment; constipation, drowsiness, urinary hesitancy or retention, tachycardia, dilation of the pupil, increased intraocular pressure, choreiform movements, weakness, vomiting, and headache. Exacerbation of parkinsonism with abrupt treatment withdrawal has been reported. Neuroleptic malignant syndrome with abrupt treatment withdrawal has been reported (See WARNINGS, Neuroleptic Malignant Syndrome).

The occurrence of angle-closure glaucoma in patients receiving trihexyphenidyl has been reported (blindness has been reported in some cases). Paradoxical sinus bradycardia, dry skin, and cycloplegia have been reported.

In addition to adverse events seen in adults, the following adverse events have been reported in the literature in pediatric patients: hyperkinesia, psychosis, forgetfulness, weight loss, restlessness, chorea, and sleep alterations.

To report SUSPECTED ADVERSE REACTIONS, contact Pharmaceutical Associates, Inc. at 1-800-845-8210 or FDA at 1-800-FDA-1088 or www.fda.gov/medwatch.

DRUG ABUSE AND DEPENDENCE

Although trihexyphenidyl is not classified as a controlled substance, the possibility of abuse should be borne in mind due to its stimulant and euphoriant properties.

OVERDOSAGE

The mean oral LD50of trihexyphenidyl has been reported to be 365 mg/kg (range, 325 to 410 mg/kg) in mice and 1660 mg/kg (1420 to 1940 mg/kg) in rats. At a dose of 40 mg/kg, dogs have exhibited emesis, restlessness followed by drowsiness, equilibrium disturbances, and mydriasis.

In humans, doses up to 300 mg (5 mg/kg) have been ingested without fatalities or sequelae. However, rare cases of death associated with trihexyphenidyl overdosages taken in conjunction with other CNS-depressant agents have been reported or in patients with a compromised respiratory condition. Trihexyphenidyl blood concentrations associated with the fatalities ranged from 0.03 to 0.80 mg/l.

Signs and Symptoms

Overdosage with trihexyphenidyl produces typical central symptoms of atropine intoxication (the central anticholinergic syndrome). Correct diagnosis depends upon recognition of the peripheral signs of parasympathetic blockade, including dilated and sluggish pupils; warm, dry skin; facial flushing; decreased secretions of the mouth, pharynx, nose, and bronchi; foul-smelling breath; elevated temperature; tachycardia, cardiac arrhythmias; decreased bowel sounds; and urinary retention. Neuropsychiatric signs such as delirium, disorientation, anxiety, hallucinations, illusions, confusion, incoherence, agitation, hyperactivity, ataxia, lip smacking and tasting movements, loss of memory, paranoia, combativeness, and seizures may be present. The condition can progress to stupor, coma, paralysis, cardiac and respiratory arrest, and death.

Treatment

Treatment of acute overdose involves symptomatic and supportive therapy. Gastric lavage or other methods to limit absorption should be instituted. A small dose of diazepam or a short-acting barbiturate may be administered if CNS excitation is observed. Phenothiazines are contraindicated because the toxicity may be intensified due to their antimuscarinic action, causing coma. Respiratory support, artificial respiration or vasopressor agents may be necessary. Hyperpyrexia must be reversed, fluid volume replaced and acid-balance maintained. Urinary catheterization may be necessary. It is not known if trihexyphenidyl is dialyzable.

DOSAGE AND ADMINISTRATION

Dosage should be individualized. The initial dose should be low and then increased gradually, especially in patients over 60 years of age. Whether trihexyphenidyl may best be given before or after meals should be determined by the way the patient reacts. Postencephalitic patients, who are usually more prone to excessive salivation, may prefer to take it after meals and may, in addition, require small amounts of atropine which, under such circumstances, is sometimes an effective adjuvant. If trihexyphenidyl tends to dry the mouth excessively, it may be better to take it before meals, unless it causes nausea. If taken after meals, the thirst sometimes induced can be allayed by mint candies, chewing gum or water.

Abrupt withdrawal of treatment for parkinsonism may result in acute exacerbation of parkinsonism symptoms; therefore, abrupt withdrawal should be avoided.

Abrupt withdrawal of treatment may result in neuroleptic malignant syndrome (NMS) (See WARNINGS).

Idiopathic Parkinsonism

As initial therapy for parkinsonism, 1 mg of trihexyphenidyl hydrochloride oral solution USP may be administered the first day. The dose may then be increased by 2 mg increments at intervals of three to five days, until a total of 6 to 10 mg is given daily. The total daily dose will depend upon what is found to be the optimal level. Many patients derive maximum benefit from this daily total of 6 to 10 mg, but some patients, chiefly those in the postencephalitic group, may require a total daily dose of 12 to 15 mg.

Drug-Induced Parkinsonism

The size and frequency of the trihexyphenidyl dose needed to control extrapyramidal reactions to commonly employed tranquilizers, notably the phenothiazines, thioxanthenes, and butyrophenones, must be determined empirically. The total daily dosage usually ranges between 5 and 15 mg although, in some cases, these reactions have been satisfactorily controlled with as little as 1 mg daily. It may be advisable to commence therapy with a single 1 mg dose. If the extrapyramidal manifestations are not controlled in a few hours, the subsequent doses may be progressively increased until satisfactory control is achieved. Satisfactory control may sometimes be more rapidly achieved by temporarily reducing the dosage of the tranquilizer when instituting trihexyphenidyl therapy and then adjusting the dosage of both drugs until the desired ataractic effect is retained without onset of extrapyramidal reactions.

It is sometimes possible to maintain the patient on a reduced trihexyphenidyl dosage after the reactions have remained under control for several days. Instances have been reported in which these reactions have remained in remission for long periods after trihexyphenidyl therapy was discontinued.

Concomitant Use with Levodopa

When trihexyphenidyl is used concomitantly with levodopa, the usual dose of each may need to be reduced. Careful adjustment is necessary, depending on side effects and degree of symptom control. A trihexyphenidyl dosage of 3 to 6 mg daily, in divided doses, is usually adequate.

Concomitant Use with Other Parasympathetic Inhibitors

Trihexyphenidyl may be substituted, in whole or in part, for other parasympathetic inhibitors. The usual technique is partial substitution initially, with progressive reduction in the other medication as the dose of trihexyphenidyl is increased.

The total daily intake of trihexyphenidyl hydrochloride oral solution USP is tolerated best if divided into 3 doses and taken at mealtimes. High doses (>10 mg daily) may be divided into 4 parts, with 3 doses administered at mealtimes and the fourth at bedtime.

HOW SUPPLIED

Trihexyphenidyl Hydrochloride Oral Solution USP, a clear, colorless, lime-mint flavored solution is supplied in the following oral dosage form:

NDC: 70518-3268-00

NDC: 70518-3268-01

NDC: 70518-3268-02

NDC: 70518-3268-03

PACKAGING: 10 in 1 BOX

PACKAGING: 12.5 mL in 1 CUP, UNIT DOSE

PACKAGING: 10 in 1 BOX

PACKAGING: 15 mL in 1 CUP, UNIT DOSE

Dispense in a tight, light-resistant container with a child-resistant closure.

STORAGE

Store at 20° to 25°C (68° to 77°F) [See USP Controlled Room Temperature].

Repackaged and Distributed By:

Remedy Repack, Inc.

625 Kolter Dr. Suite #4 Indiana, PA 1-724-465-8762

DO NOT FREEZE.

Repackaged and Distributed By:

Remedy Repack, Inc.

625 Kolter Dr. Suite #4 Indiana, PA 1-724-465-8762

PACKAGE LABEL

DRUG: Trihexyphenidyl Hydrochloride

GENERIC: Trihexyphenidyl Hydrochloride

DOSAGE: SOLUTION

ADMINSTRATION: ORAL

NDC: 70518-3268-0

NDC: 70518-3268-1

NDC: 70518-3268-2

NDC: 70518-3268-3

FLAVOR: LIME

PACKAGING: 12.5 mL in 1 CUP, UNIT-DOSE

OUTER PACKAGING: 10 in 1 BOX

PACKAGING: 15 mL in 1 CUP, UNIT DOSE

PACKAGING: 10 in 1 BOX

ACTIVE INGREDIENT(S):

- TRIHEXYPHENIDYL HYDROCHLORIDE 2mg in 5mL

INACTIVE INGREDIENT(S):

- PROPYLPARABEN
- WATER
- SODIUM CHLORIDE
- ALCOHOL
- METHYLPARABEN
- ANHYDROUS CITRIC ACID
- SORBITOL SOLUTION